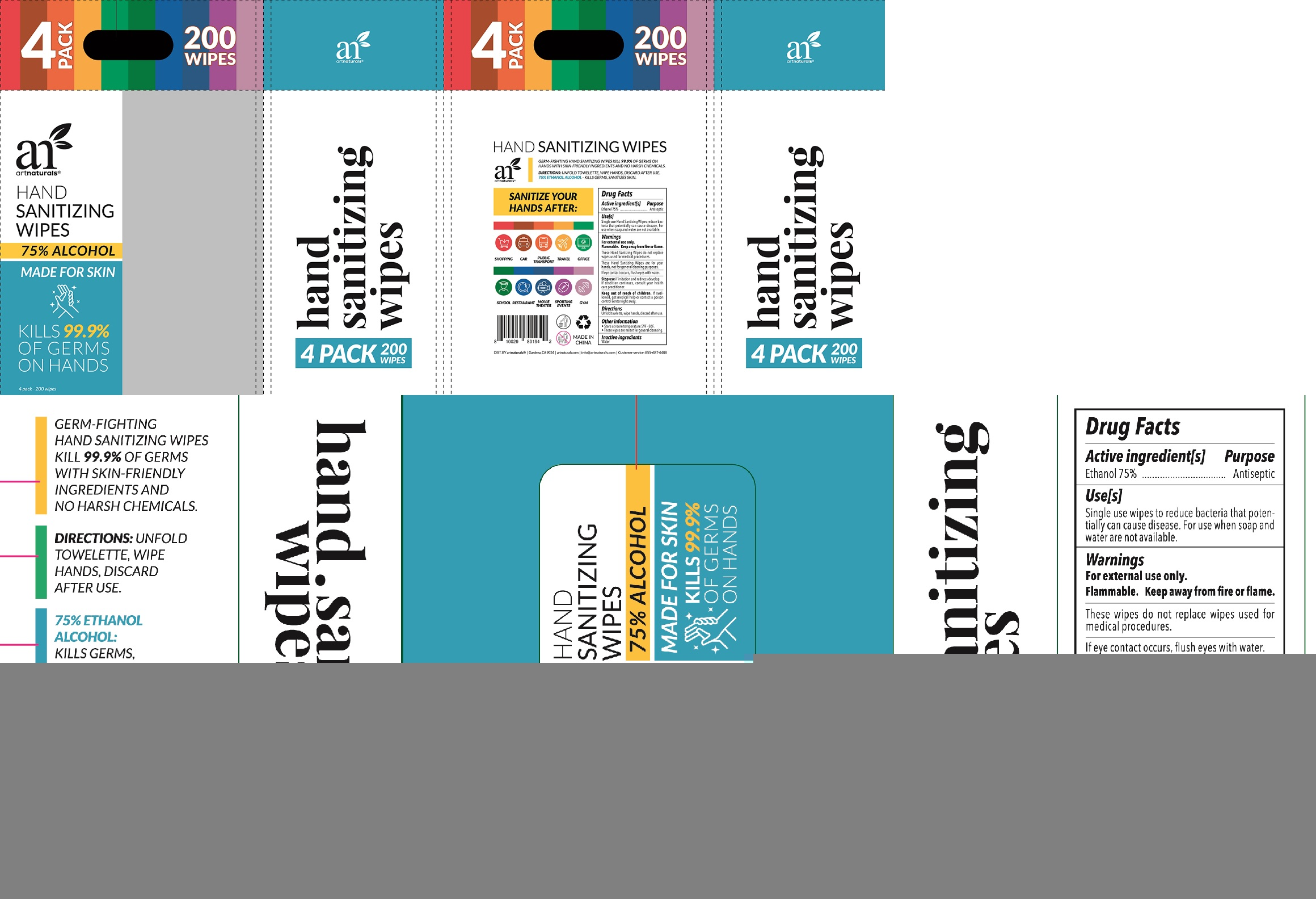 DRUG LABEL: Hand Sanitizing Wipes
NDC: 42129-201 | Form: CLOTH
Manufacturer: Fustin(Xiamen) Commodity Co., ltd
Category: otc | Type: HUMAN OTC DRUG LABEL
Date: 20201120

ACTIVE INGREDIENTS: ALCOHOL 75 1/100 1
INACTIVE INGREDIENTS: WATER

Alcohol wipes

Active Ingredient

Ethanol 75%

Purpose

Antiseptic

Warnings

For external use only.
Flammable. Keep away from fire or flame.
These wipes do not replace wipes used for medical procedures.

When using this product, if eye contact occurs, flush eyes with water.

Stop use and ask a doctor if irritation and redness develop. If condition continues, consult your health care practitioner.

Other information

- Store at room tmperature 59℉-86℉.
- These wipes are meant for general cleansing.

INDICATIONS AND USAGE

Single use wipes to reduce bacteria that potentially can cause disease. For use when soap and water are not available.

Keep out of reach of children. If swallowed, get medical help or contact a Poison Control Center right away.

Directions

Unfold towlette, wipe hands, discard after use.

Inactive ingredients

Water